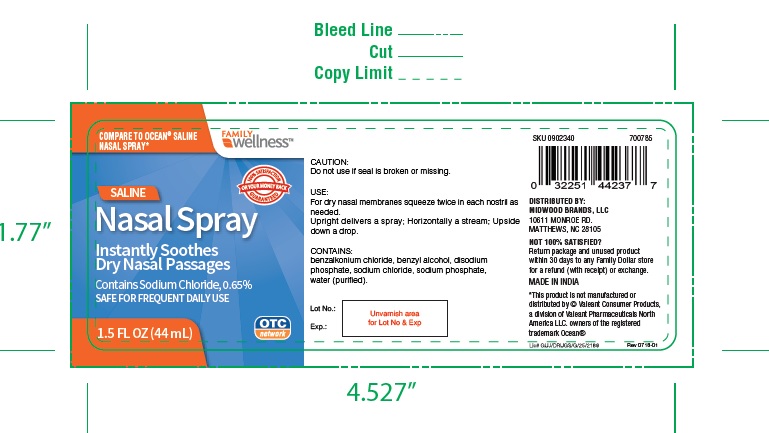 DRUG LABEL: Saline Nasal
NDC: 76168-602 | Form: SPRAY
Manufacturer: Velocity Pharma LLC
Category: otc | Type: HUMAN OTC DRUG LABEL
Date: 20191119

ACTIVE INGREDIENTS: SODIUM CHLORIDE 6.5 mg/1 mL
INACTIVE INGREDIENTS: BENZALKONIUM CHLORIDE; SODIUM PHOSPHATE, DIBASIC, ANHYDROUS; BENZYL ALCOHOL; SODIUM PHOSPHATE, MONOBASIC, ANHYDROUS; WATER

Saline Nasal Spray

Active ingredient

Sodium Chloride, 0.65%

Purpose

Moisturizer

Uses

For dry nasal membranes

Warnings

Do not use if seal is broken or missing.

Keep out of reach of children. The use of this dispenser by more than one person may spread infection.

Directions

- Squeeze twice in each nostril as needed
- Upright delivers a spray, horizontally a stream, upside down a drop

Inactive ingredients

Benzalkonium chloride, Disodium phosphate, Phenylcarbinol, Monosodium phosphate, Water